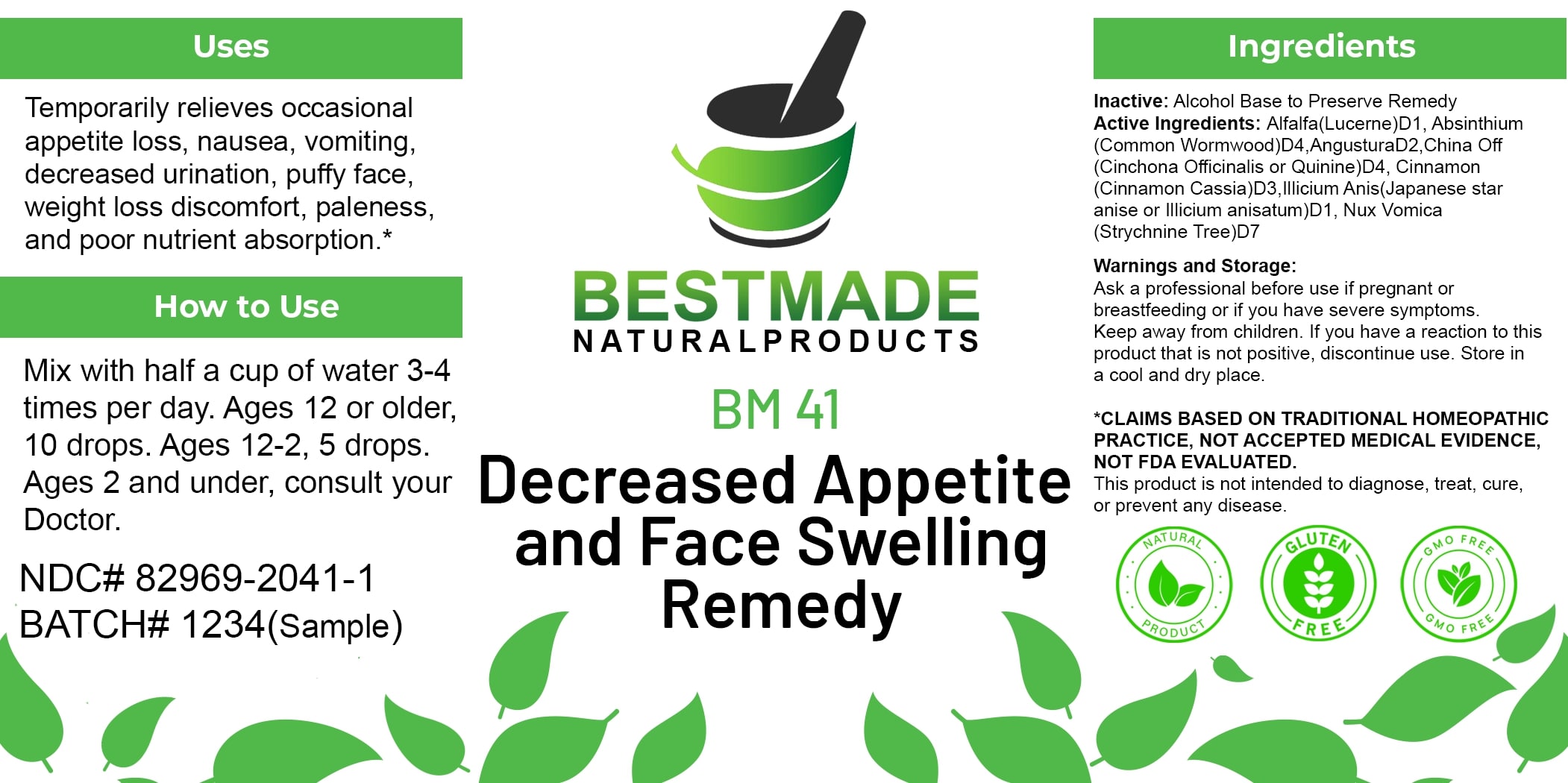 DRUG LABEL: Bestmade Natural Products BM41
NDC: 82969-2041 | Form: LIQUID
Manufacturer: Bestmade Natural Products
Category: homeopathic | Type: HUMAN OTC DRUG LABEL
Date: 20250123

ACTIVE INGREDIENTS: ALFALFA 30 [hp_C]/30 [hp_C]; WORMWOOD 30 [hp_C]/30 [hp_C]; ANGOSTURA BARK 30 [hp_C]/30 [hp_C]; STRYCHNOS NUX-VOMICA SEED 30 [hp_C]/30 [hp_C]; STAR ANISE 30 [hp_C]/30 [hp_C]; CINCHONA OFFICINALIS BARK 30 [hp_C]/30 [hp_C]; CINNAMON 30 [hp_C]/30 [hp_C]
INACTIVE INGREDIENTS: ALCOHOL 30 [hp_C]/30 [hp_C]

BM41

DOSAGE AND ADMINISTRATION

How to Use

Mix with half a cup of water 3-4 times per day. Ages 12 or older, 10 drops. Ages 12-2, 5 drops. Ages 2 and under, consult your Doctor.

Uses

Temporarily relieves occasional appetite loss, nausea, vomiting, decreased urination, puffy face, weight loss discomfort, paleness, and poor nutrient absorption.*

*CLAIMS BASED ON TRADITIONAL HOMEOPATHIC PRACTICE, NOT ACCEPTED MEDICAL EVIDENCE, NOT FDA EVALUATED.

This product is not intended to diagnose, treat, cure, or prevent any disease.

Uses

Temporarily relieves occasional appetite loss, nausea, vomiting, decreased urination, puffy face, weight loss discomfort, paleness, and poor nutrient absorption.*

*CLAIMS BASED ON TRADITIONAL HOMEOPATHIC PRACTICE, NOT ACCEPTED MEDICAL EVIDENCE, NOT FDA EVALUATED.

This product is not intended to diagnose, treat, cure, or prevent any disease.

INACTIVE INGREDIENT

Ingredients

Inactive: Alcohol Base to Preserve Remedy

ACTIVE INGREDIENT

Active Ingredients: Alfalfa (Lucerne) D1, Absinthium (Common Wormwood) D4, Angustura D2, China Off (Cinchona Officinalis or Quinine) D4, Cinnamon (Cinnamon Cassia) D3, Illicium Anis (Japanese star anise or Illicium anisatum) D1, Nux Vomica (Strychnine Tree) D7

KEEP OUT OF REACH OF CHILDREN

Warnings and Storage:

Ask a professional before use if pregnant or breastfeeding or if you have severe symptoms. Keep away from children. If you have a reaction to this product that is not positive, discontinue use. Store in a cool and dry place.

Warnings and Storage:

Ask a professional before use if pregnant or breastfeeding or if you have severe symptoms. Keep away from children. If you have a reaction to this product that is not positive, discontinue use. Store in a cool and dry place.

*CLAIMS BASED ON TRADITIONAL HOMEOPATHIC PRACTICE, NOT ACCEPTED MEDICAL EVIDENCE, NOT FDA EVALUATED.

This product is not intended to diagnose, treat, cure, or prevent any disease.

Entire package label